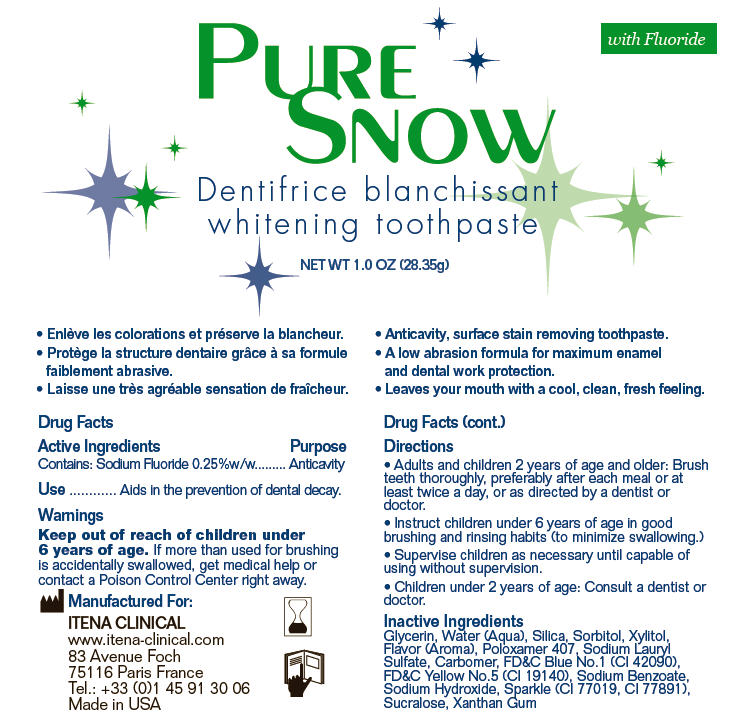 DRUG LABEL: Pure Snow whitening
NDC: 52893-001 | Form: GEL, DENTIFRICE
Manufacturer: Itena Clinical
Category: otc | Type: HUMAN OTC DRUG LABEL
Date: 20121129

ACTIVE INGREDIENTS: Sodium Fluoride 0.07 g/28.35 g
INACTIVE INGREDIENTS: Glycerin; Water; Silicon Dioxide; Sorbitol; Xylitol; Methyl Salicylate; Poloxamer 407; Sodium Lauryl Sulfate; FD&C Blue No. 1; FD&C Yellow No. 5; Sodium Benzoate; Sodium Hydroxide; Sucralose; Xanthan Gum

Pure Snow whitening toothpaste

Drug Facts

Active Ingredients

Contains: Sodium Fluoride 0.25%w/w

Purpose

Anticavity

Use

Aids in the prevention of dental decay.

Warnings

Keep out of reach of children under 6 years of age. If more than used for brushing is accidentally swallowed, get medical help or contact a Poison Control Center right away.

Directions

- Adults and children 2 years of age and older: Brush teeth thoroughly, preferably after each meal or at least twice a day, or as directed by a dentist or doctor.
- Instruct children under 6 years of age in good brushing and rinsing habits (to minimize swallowing.)
- Supervise children as necessary until capable of using without supervision.
- Children under 2 years of age: Consult a dentist or doctor.

Inactive Ingredients

Glycerin, Water (Aqua), Silica, Sorbitol, Xylitol, Flavor (Aroma), Poloxamer 407, Sodium Lauryl Sulfate, Carbomer, FD&C Blue No.1 (CI 42090), FD&C Yellow No.5 (CI 19140), Sodium Benzoate, Sodium Hydroxide, Sparkle (CI 77019, CI 77891), Sucralose, Xanthan Gum

Manufactured For:
ITENA CLINICAL
www.itena-clinical.com
83 Avenue Foch
75116 Paris France

PRINCIPAL DISPLAY PANEL - 28.35 g Tube Label

PURE
SNOW

with Fluoride

whitening toothpaste

NET WT 1.0 OZ (28.35g)